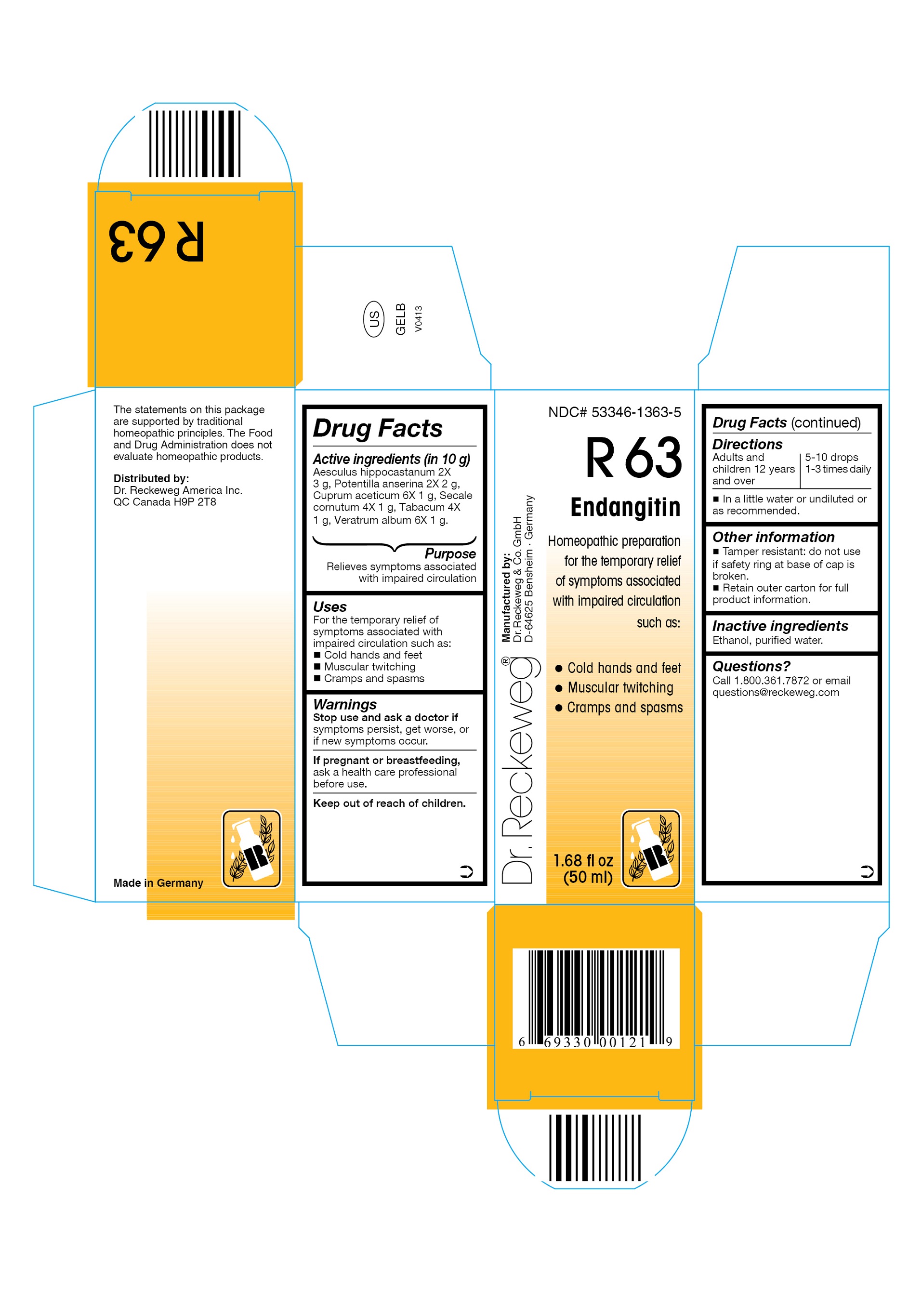 DRUG LABEL: DR. RECKEWEG R63 Endangitin
NDC: 53346-1363 | Form: LIQUID
Manufacturer: PHARMAZEUTISCHE FABRIK DR. RECKEWEG & CO
Category: homeopathic | Type: HUMAN OTC DRUG LABEL
Date: 20130404

ACTIVE INGREDIENTS: HORSE CHESTNUT 2 [hp_X]/50 mL; POTENTILLA ANSERINA FLOWERING TOP 2 [hp_X]/50 mL; CUPRIC ACETATE 6 [hp_X]/50 mL; CLAVICEPS PURPUREA SCLEROTIUM 4 [hp_X]/50 mL; TOBACCO LEAF 4 [hp_X]/50 mL; VERATRUM ALBUM ROOT 6 [hp_X]/50 mL
INACTIVE INGREDIENTS: ALCOHOL; WATER

DR. RECKEWEG R63 Endangitin

Active ingredients
Aesculus hippocastanum 2X 3 g, Potentilla anserina 2X 2 g, Cuprum aceticum 6X 1 g, Secale cornutum 4X 1 g, Tabacum 4X 1 g, Veratrum album 6X 1 g in 10 g.

Purpose
Relieves symptoms associated with impaired circulation

Uses
For the temporary relief of symptoms associated with impaired circulation such as:

- Cold hands and feet
- Muscular twitching
- Cramps and spasms

Warnings

Stop use and ask a doctor if symptoms persist, get worse, or if new symptoms occur.

PREGNANCY OR BREAST FEEDING

If pregnant or breastfeeding, ask a health care professional before use.

Keep out of reach of children.

Directions
Adults and children ≥ 12 years 5-10 drops 1-3 times daily in a little water or undiluted or as recommended.

Other information

- Tamper resistant: do not use if safety ring at base of cap is broken.
- Retain outer carton for full product instructions.

Inactive ingredients
Ethanol, purified water.

Questions?
Call 1-800-361-7872 or email questions@reckeweg.com

PACKAGE LABEL

NDC# 53346-1363-5
Dr. Reckeweg R63 Endangitin
Homeopathic preparation for the temporary relief of symptoms associated with impaired circulation such as:

- Cold hands and feet
- Muscular twitching
- Cramps and spasms

Manufactured by:
Dr. Reckeweg Co. GmbH
D-64625 Bensheim
Germany
1.68 fl oz
(50 ml)